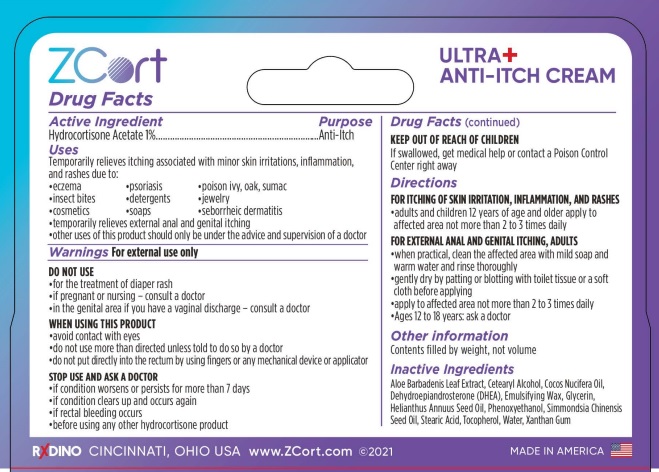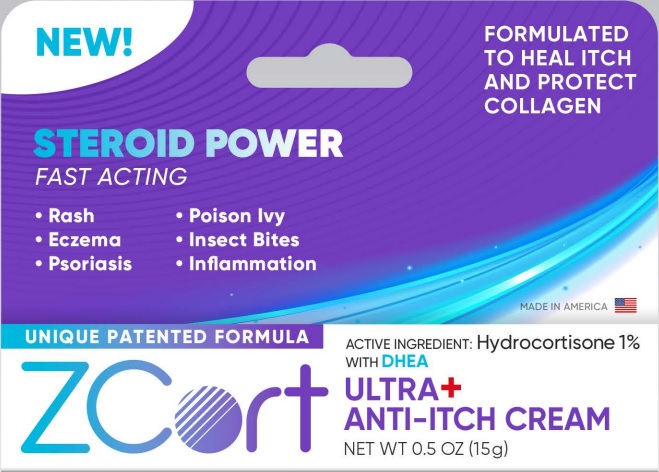 DRUG LABEL: ZCort

NDC: 81335-532 | Form: CREAM
Manufacturer: RxDino, LLC
Category: otc | Type: HUMAN OTC DRUG LABEL
Date: 20250129

ACTIVE INGREDIENTS: HYDROCORTISONE ACETATE 10 mg/1 g
INACTIVE INGREDIENTS: PHENOXYETHANOL; PRASTERONE; ALOE VERA LEAF; POLYSORBATE 60; TOCOPHEROL; STEARIC ACID; COCONUT OIL; JOJOBA OIL; WATER; SUNFLOWER OIL; XANTHAN GUM; GLYCERIN; CETOSTEARYL ALCOHOL

Drug Facts Active Ingredients

Hydrocortisone Acetate 1%

Purpose

Anti-Itch

Uses

Temporarily relieves itching associated with minor skin irritations, inflammation, and rashes due to:

- Eczema
- psoriasis
- poison ivy, oak, sumac
- insect bites
- detergents
- jewelry
- cosmetics
- soaps
- seborrheic dermatitis
- temporarily relieves external anal and genital itching
- other uses of this product should only be under the advice and supervision of a doctor

Warnings

For external use only

DO NOT USE

- for the treatment of diaper rash
- if pregnant or nursing - consult a doctor
- in the genital area if you have a vaginal discharge - consult a doctor

WHEN USING THIS PRODUCT

- avoid contact with eyes
- do not use more than directed unless told to do so by a doctor
- do not put directly into the rectum by using fingers or any mechanical device or applicator

STOP USE AND ASK A DOCTOR

- if condition worsens or persists for more than 7 days
- if condition clears up and occurs again
- if rectal bleeding occurs
- before using any other hydrocortisone product

KEEP OUT OF REACH OF CHILDREN

If swallowed, get medical help or contact a Poison Control Center right away

Directions

FOR ITCHING OF SKIN IRRITATION, INFLAMMATION, AND RASHES

- adults and children 12 years of age and older apply to affected area not more than 2 to 3 times daily

FOR EXTERNAL ANAL AND GENITAL ITCHING, ADULTS

- when practical, clean the affected area with mild soap and warm water and rinse thoroughly
- gently dry by patting or blotting with toilet tissue or a soft cloth before applying
- apply to affected area not more than 2 to 3 times daily
- Ages 12 to 18 years: ask a doctor

Other Information

Contents filled by weight, not volume

Inactive Ingredients

Aloe Barbadenis Leaf Extract, Cetearyl Alcohol, Cocos Nucifera Oil, Dehydroepiandrosterone (DHEA), Emulsifying Wax, Glycerin, Helianthus Annuus Seed Oil, Phenoxyethanol, Simmondsia Chinensis Seed Oil, Stearic Acid, Tocopherol, Water, Xanthan Gum

Front Display Panel and Back Card

NEW!

FORMULATED TO HEAL ITCH AND PROTECT COLLAGEN

STEROID POWER

FAST ACTING

- Rash
- Poison Ivy
- Eczema
- Insect Bites
- Psoriasis
- Inflammation

UNIQUE PATENTED FORMULA

ZCort ULTRA+ ANTI-ITCH CREAM

NET WT 0.5 OZ (15g)

ACTIVE INGREDIENT: HYDROCORTIZONE 1% WITH DHEA

see zcortfront.jpg

ZCort Ultra+ ANTI-ITCH CREAM BACK CARD

see zcortbackbox.jpg